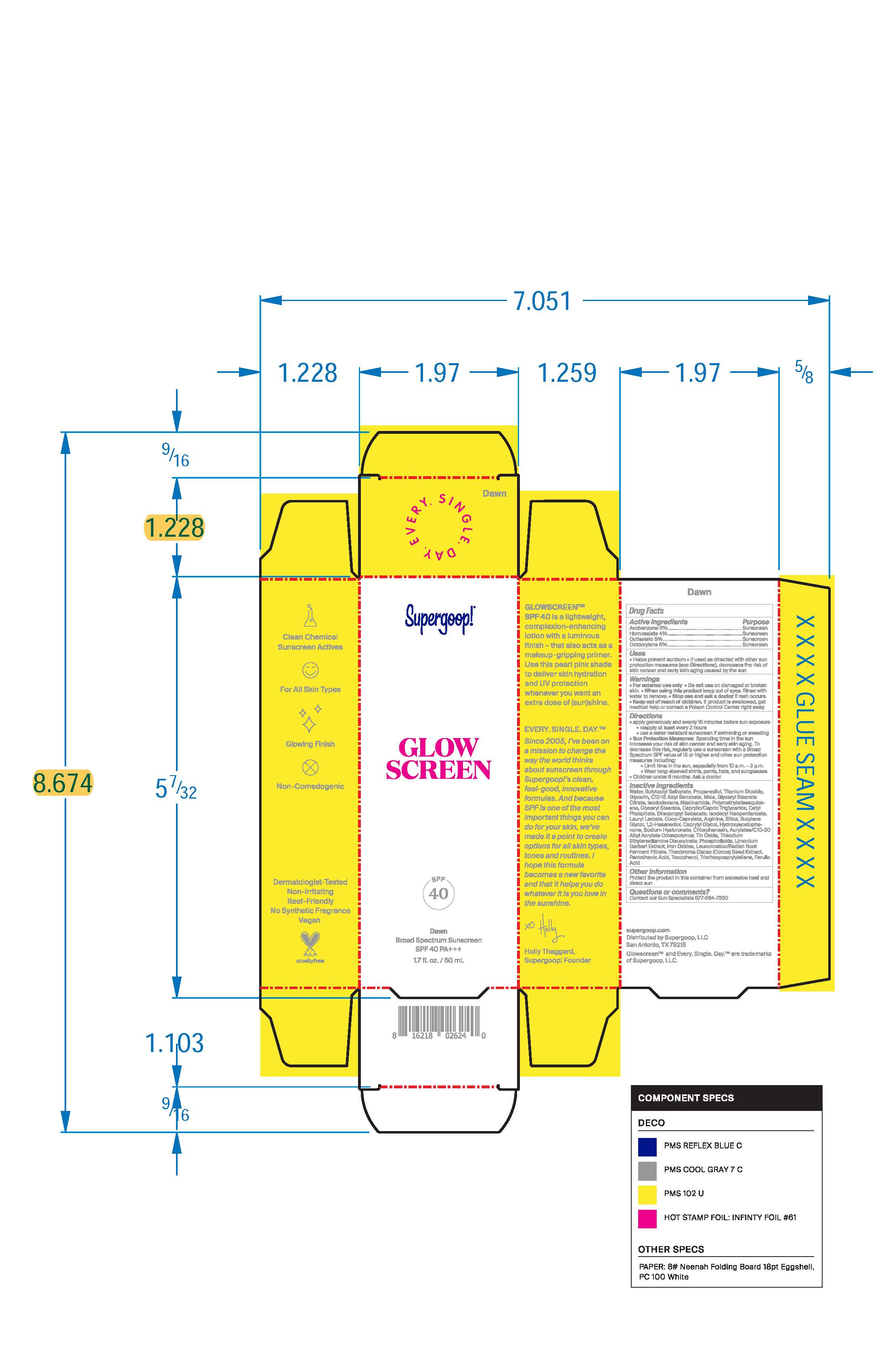 DRUG LABEL: Glowscreen SPF 40 - Dawn
NDC: 75936-606 | Form: LOTION
Manufacturer: Supergoop, LLC
Category: otc | Type: HUMAN OTC DRUG LABEL
Date: 20241205

ACTIVE INGREDIENTS: AVOBENZONE 3 g/100 mL; OCTISALATE 5 g/100 mL; HOMOSALATE 4 g/100 mL; OCTOCRYLENE 8 g/100 mL
INACTIVE INGREDIENTS: BROWN IRON OXIDE; BUTYLENE GLYCOL; THEOBROMA CACAO WHOLE; LIMONIUM GERBERI FLOWERING TOP; WATER O-18; CAPRYLIC/CAPRIC/PALMITIC/STEARIC TRIGLYCERIDE; TITANIUM DIOXIDE; GLYCERYL STEARATE CITRATE; ISODODECANE; GLYCERIN; COCO-CAPRYLATE; PANTOTHENIC ACID; TRIETHOXYCAPRYLYLSILANE; FERULIC ACID; NIACINAMIDE; POLYMETHYLSILSESQUIOXANE (11 MICRONS); STANNIC OXIDE; TRISODIUM ETHYLENEDIAMINE DISUCCINATE; PEG-120 GLYCERYL STEARATE; LAURYL LACTATE; PROPANEDIOL; BUTYLOCTYL SALICYLATE; SILICA, TRIMETHYLSILYL CAPPED; 1,2-HEXANEDIOL; CAPRYLYL GLYCOL; GR-270773 PHOSPHOLIPID EMULSION; HELIANTHUS ANNUUS SEED WAX; CHLORPHENESIN; CETYL PHOSPHATE; DIISOPROPYL SEBACATE; ISODECYL NEOPENTANOATE; ALKYL (C12-15) BENZOATE; MICA; ARGININE; TOCOPHEROL; ACRYLATES CROSSPOLYMER-6; HYDROXYACETOPHENONE; PEG-9 DIGLYCIDYL ETHER/SODIUM HYALURONATE CROSSPOLYMER; LEUCONOSTOC/RADISH ROOT FERMENT FILTRATE

Active Ingredients Purpose

Avobenzone 3%.......................................Sunscreen

Homosalate 4%.......................................Sunscreen

Octisalate 5%.......................................Sunscreen

Octocrylene 8%.......................................Sunscreen

PURPOSE

Helps prevent sunburn

If used as directed with other sun protection measures (see Directions), decreases the risk of skin cancer and early skin aging caused by the sun

Keep out of reach of children. If product is swallowed, get medical help, or contact a poison control center right away.

WARNINGS

For External use only

Do not use on damaged or broken skin

When using this product, keep out of eyes. Rinse with water to remove

Stop use and ask a doctor if rash occurs

Directions

Apply generously and evenly 15 minutes before sun exposure

Reapply at least every 2 hours

Use a water resistant sunscreen if swimming or sweating

Sun Protection Measures: Spending time in the sun increases your risk of skin cancer and early skin aging. To decrease this risk, regularly use a sunscreen with a Broad Spectrum SPF value of 15 or higher and other sun protection measures including:

Limit time in the sun, especially from 10 a.m.- 2 p.m.

Wear long-sleeved shirts, pants, hats, and sunglasses

Children under 6 months: Ask a doctor

INACTIVE INGREDIENT

Water, Butyloctyl Salicylate, Propanediol, Titanium Dioxide, Glycerin, C12-15 Alkyl Benzoate, Mica, Glyceryl Stearate Citrate, Isododecane, Niacinamide, Polymethylsilsesquioxane, Glyceryl Stearate, Caprylic/Capric Triglyceride, Cetyl Phosphate, Diisopropyl Sebacate, Isodecyl Neopentanoate, Lauryl Lactate, Coco-Caprylate, Arginine, Silica, Butylene Glycol, 1,2-Hexanediol, Caprylyl Glycol, Hydroxyacetophenone, Sodium Hyaluronate, Chlorphenesin, Acrylates/C10-30 Alkyl Acrylate Crosspolymer, Tin Oxide, Trisodium Ethylenediamine Disuccinate, Phospholipids, Limonium Gerberi Extract, Iron Oxides, Leuconostoc/Radish Root Ferment Filtrate, Theobroma Cacao (Cocoa) Seed Extract, Pantothenic Acid, Tocopherol, Triethoxycaprylylsilane, Ferulic Acid

PACKAGE LABEL

SPF 40
Dawn
Broad Spectrum Sunscreen SPF 40 PA+++

1.7 fl. oz. / 50 mL